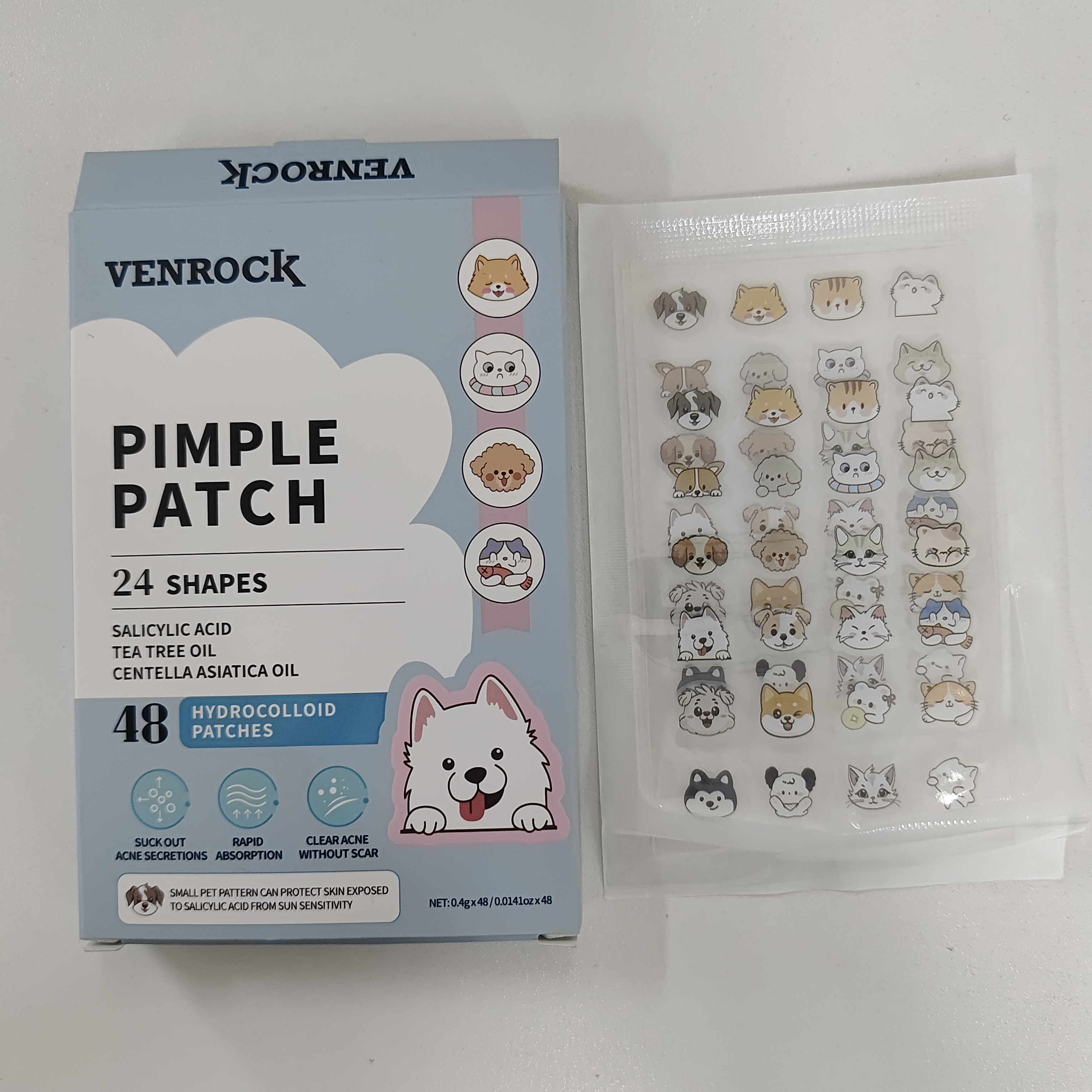 DRUG LABEL: VENROCK
NDC: 85772-0001 | Form: PATCH
Manufacturer: Guangzhou Oupeng Cosmetics Co., Ltd.
Category: otc | Type: HUMAN OTC DRUG LABEL
Date: 20250605

ACTIVE INGREDIENTS: SALICYLIC ACID 1.5 g/100 g
INACTIVE INGREDIENTS: POLYURETHANE-34 (55 MPA, TENSILE STRENGTH OF FILM AT BREAK) 35 g/100 g; POLYETHYLENE TEREPHTHALATE (INTRINSIC VISCOSITY 0.40-0.70) 6.5 g/100 g; CENTELLA ASIATICA 1.5 g/100 g; STYRENE/ACRYLAMIDE COPOLYMER (MW 500000) 25 g/100 g; DIETHYLHEXYL ADIPATE 11 g/100 g; DIMETHICONE 10 g/100 g; CELLULOSE GUM 8 g/100 g; MELALEUCA ALTERNIFOLIA (TEA TREE) LEAF OIL 1.5 g/100 g

Active ingredient (in each dosage unit)

Salicylic Acid 1.5%

Purpose

Acne treatment

Uses

- For the treatment of acne
- Helps clear up pimples and blackheads
- Helps prevent new acne pimples from forming

Warnings

For external use only

When using this product

Avoid using with other irritating products: such as products containing retinoic acid, fruit acid and other ingredients, so as not to cause excessive irritation to the skin

Ask a doctor or pharmacist before use if you have

- Sensitive skin
- Severe acne

When using this product

- Avoid contact with eyes, lips, and mouth. If contact occurs, rinse thoroughly with water
- Skin irritation and dryness is more likely to occur if you use another topical acne medication at the same time. If irritation occurs, only use one topical acne medication at a time
- Mild irritation such as redness, burning, itching, peeling, or dryness may occur
- Avoid unnecessary sun exposure

Stop use and ask a doctor if

- Skin irritation becomes severe or worsens
- Rash or allergic reaction develops
- Your condition does not improve after 7 days of use

PREGNANCY OR BREAST FEEDING SECTION

If pregnant or breast-feeding, ask a health professional before use

Keep out of reach of children

In case of accidental ingestion, get medical help or contact a Poison Control Center right away.

Directions

- Cleanse the skin thoroughly before applying medication
- Cover the entire affected area with a patch one to two times daily
- Because excessive drying of the skin may occur, start with one application daily, then gradually increase to two times daily if needed or as directed by a doctor
- If bothersome dryness or peeling occurs, reduce application to once a day or every other day
- 6-8 hours remove patch after

Other information

- Store at room temperature 15°-30°C (59°-86°F)
- Protect from excessive heat and direct sun

Inactive ingredients

POLYURETHANE-34, STYRENE/ACRYLAMIDE COPOLYMER, DIMETHICONE, DIETHYLHEXYL ADIPATE, CELLULOSE GUM, POLYETHYLENE TEREPHTHALATE, SALICYLIC ACID, CENTELLA ASIATICA, MELALEUCA ALTERNIFOLIA (TEA TREE) LEAF OIL

Questions?

934-935-7135 / Yiqinzhi726@gmail.com

Box Front Panel

VENROCK
PIMPLE PATCH
24 SHAPES
SALICYLIC ACID
TEA TREE OIL
CENTELLA ASIATICA OIL
48 HYDROCOLLOID PATCHES
SUCK OUT ACNE SECRETIONS
RAPID ABSORPTION
CLEAR ACNE WITHOUT SCAR
SMALL PET PATTERN CAN PROTECT SKIN EXPOSED TO SALICYLIC ACID FROM SUN SENSITIVITY
NET: 0.4g x 48 / 0.0141oz x 48